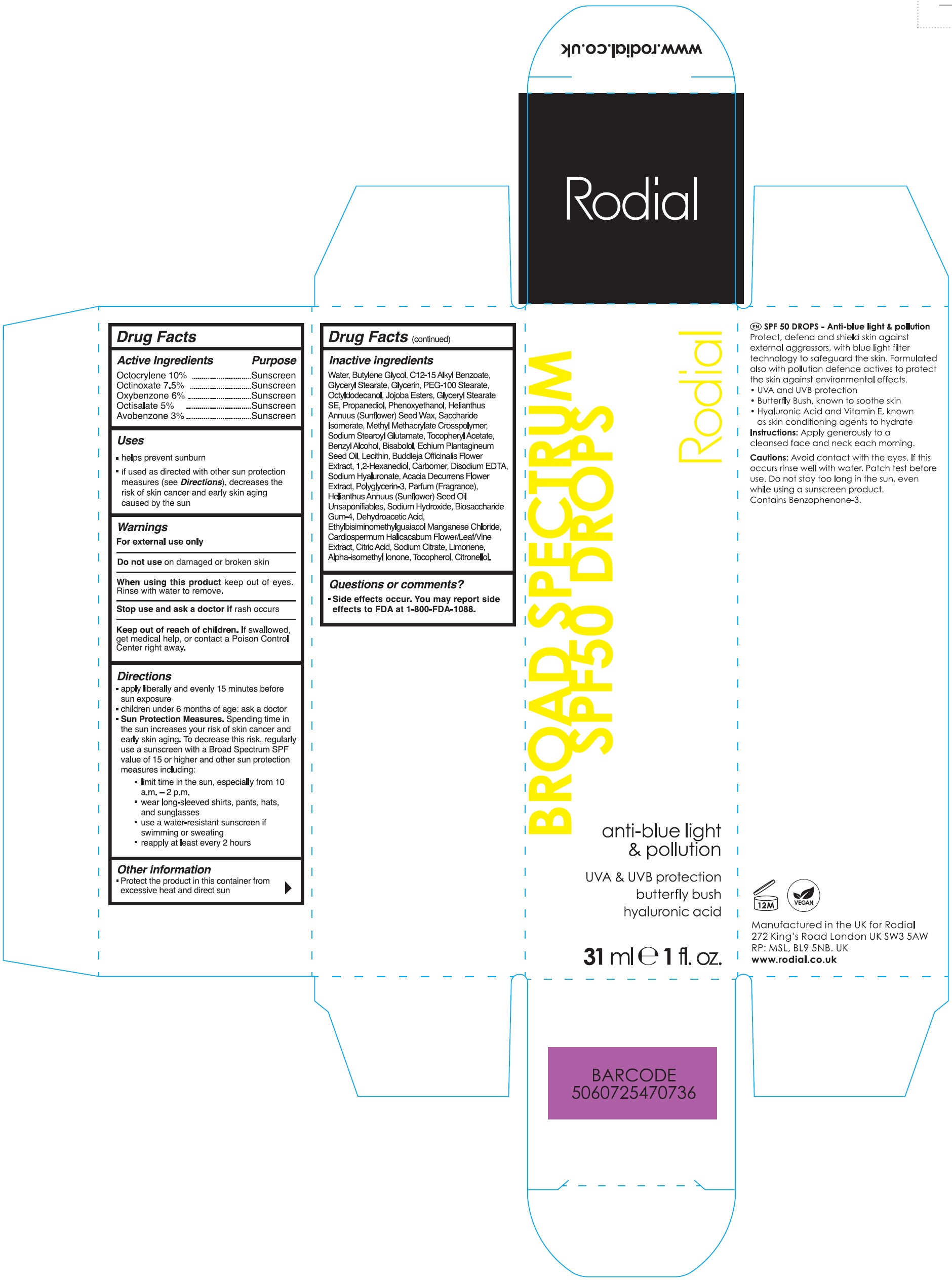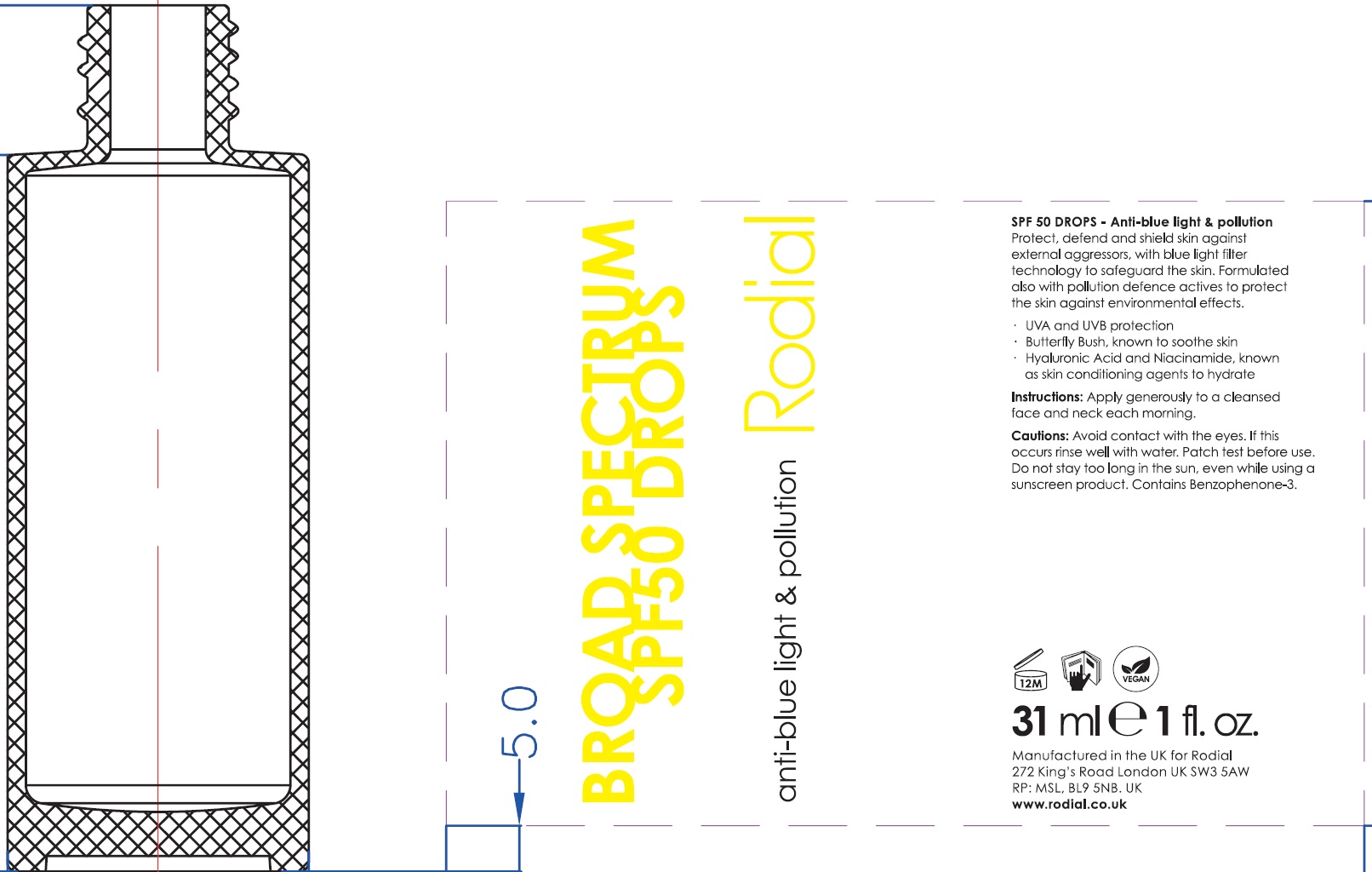 DRUG LABEL: Rodial Broad Spectrum SPF 50 Drops Anti-Blue Light and Pollution
NDC: 52456-022 | Form: LOTION
Manufacturer: Rodial Ltd.
Category: otc | Type: HUMAN OTC DRUG LABEL
Date: 20231110

ACTIVE INGREDIENTS: OCTOCRYLENE 100 mg/1 mL; OCTINOXATE 75 mg/1 mL; OXYBENZONE 60 mg/1 mL; OCTISALATE 50 mg/1 mL; AVOBENZONE 30 mg/1 mL
INACTIVE INGREDIENTS: WATER; BUTYLENE GLYCOL; ALKYL (C12-15) BENZOATE; GLYCERYL MONOSTEARATE; GLYCERIN; PEG-100 STEARATE; OCTYLDODECANOL; GLYCERYL STEARATE SE; PROPANEDIOL; PHENOXYETHANOL; HELIANTHUS ANNUUS SEED WAX; SACCHARIDE ISOMERATE; METHYL METHACRYLATE/GLYCOL DIMETHACRYLATE CROSSPOLYMER; SODIUM STEAROYL GLUTAMATE; .ALPHA.-TOCOPHEROL ACETATE; BENZYL ALCOHOL; LEVOMENOL; ECHIUM PLANTAGINEUM SEED OIL; 1,2-HEXANEDIOL; CARBOMER HOMOPOLYMER, UNSPECIFIED TYPE; EDETATE DISODIUM ANHYDROUS; HYALURONATE SODIUM; ACACIA DECURRENS FLOWER; POLYGLYCERIN-3; HELIANTHUS ANNUUS FLOWERING TOP; SODIUM HYDROXIDE; BIOSACCHARIDE GUM-4; DEHYDROACETIC ACID; ETHYLBISIMINOMETHYLGUAIACOL MANGANESE CHLORIDE; CARDIOSPERMUM HALICACABUM FLOWERING TOP; CITRIC ACID MONOHYDRATE; SODIUM CITRATE; LIMONENE, (+)-; ISOMETHYL-.ALPHA.-IONONE; TOCOPHEROL; .BETA.-CITRONELLOL, (R)-; JOJOBA OIL; BUDDLEJA OFFICINALIS FLOWER; LECITHIN, SOYBEAN

Rodial Broad Spectrum SPF 50 Drops Anti-Blue Light & Pollution

Active Ingredients

Octocrylene 10% Octinoxate 7.5% Oxybenzone 6% Octisalate 5% Avobenzone 3%

Purpose

Sunscreen

Uses

- helps prevent sunburn
- if used as directed with other sun protection measures (see), decreases the risk of skin cancer and early skin aging caused by the sun Directions

Warnings

For external use only

Do not use

on damaged or broken skin

When using this product

keep out of eyes. Rinse with water to remove.

Stop use and ask a doctor

if rash occurs

Keep out of reach of children.

If swallowed, get medical help, or contact a Poison Control Center right away.

Directions

- apply liberally and evenly 15 minutes before sun exposure
- children under 6 months of age: ask a doctor
- Spending time in the sun increases your risk of skin cancer and early skin aging. To decrease this risk, regularly use a sunscreen with a Broad Spectrum SPF value of 15 or higher and other sun protection measures including: Sun Protection Measures.
- limit time in the sun, especially from 10 a.m. - 2 p.m.
- wear long-sleeved shirts, pants, hats, and sunglasses
- use a water-resistant sunscreen if swimming or sweating
- reapply at least every 2 hours

Other information

- Protect the product in this container from excessive heat and direct sun

Inactive ingredients

Water, Butylene Glycol, C12-15 Alkyl Benzoate, Glyceryl Stearate, Glycerin, PEG -100 Stearate, Octyldodecanol, Jojoba Esters, Glyceryl Stearate SE, Propanediol, Phenoxyethanol, Helianthus Annuus (Sunflower) Seed Wax, Saccharide Isomerate, Methyl Methacrylate Crosspolymer, Sodium Stearoyl Glutamate, Tocopheryl Acetate, Benzyl Alcohol, Bisabolol, Echium Plantagineum Seed Oil, Lecithin, Buddleja Officinalis Flower Extract, 1,2-Hexanediol, Carbomer, Disodium EDTA, Sodium Hyaluronate, Acacia Decurrens Flower Extract, Polyglycerin-3, Parfum (Fragrance), Helianthus Annuus (Sunflower) Seed Oil Unsaponifiables, Sodium Hydroxide, Biosaccharide Gum-4, Dehydroacetic Acid, Ethylbisiminomethylguaiacol Manganese Chloride, Cardiospermum Halicacabum Flower/Leaf/Vine Extract, Citric Acid, Sodium Citrate, Limonene, Alpha-isomethyl Ionone, Tocopherol, Citronellol.

Questions or comments?

- Side effects occur. You may report side effects to FDA at 1-800-FDA-1088.